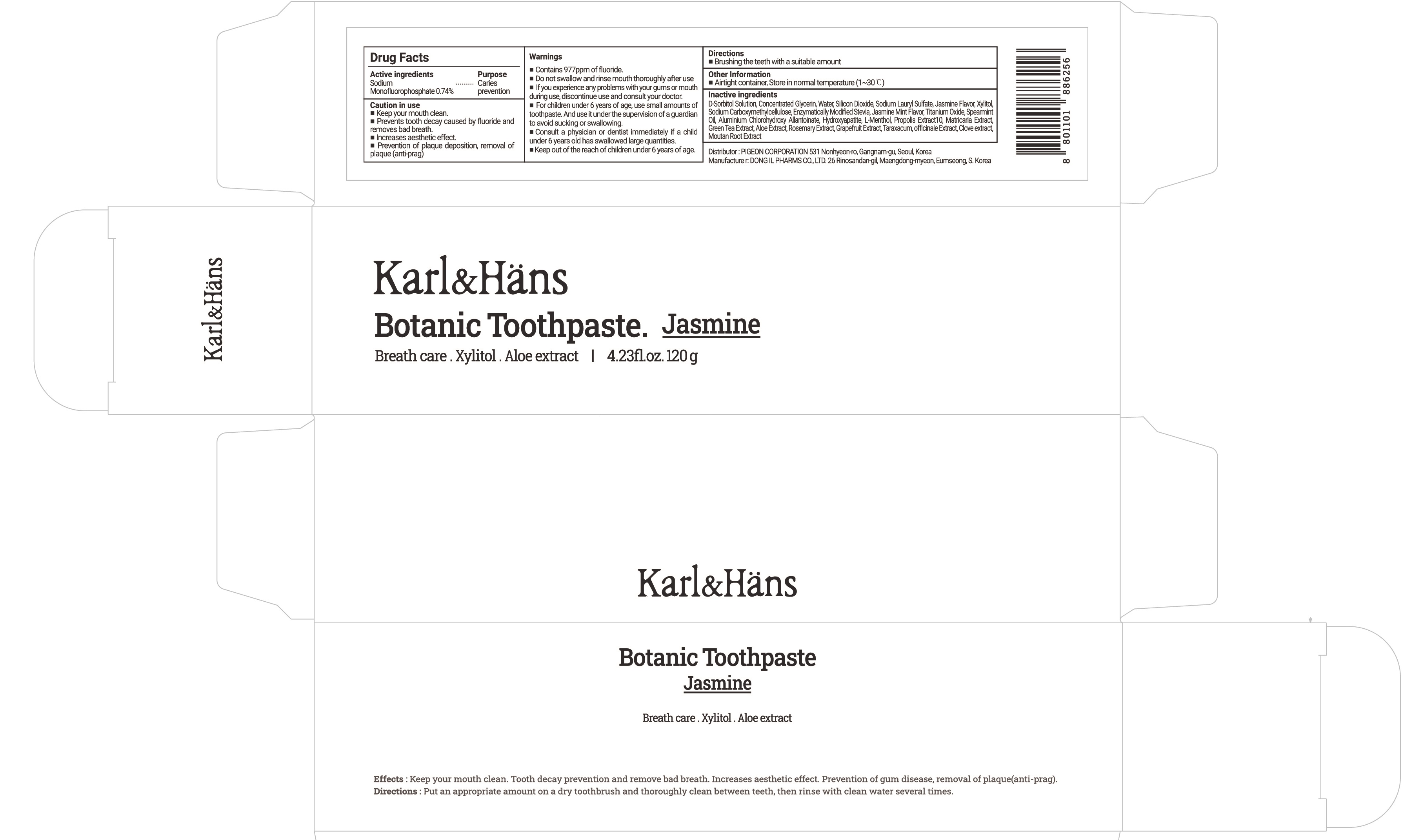 DRUG LABEL: Karl and Hans Botanic Jasmine
NDC: 78151-060 | Form: PASTE, DENTIFRICE
Manufacturer: PIGEON CORPORATION
Category: otc | Type: HUMAN OTC DRUG LABEL
Date: 20240808

ACTIVE INGREDIENTS: SODIUM MONOFLUOROPHOSPHATE 0.74 g/100 g
INACTIVE INGREDIENTS: SORBITOL; GLYCERIN; WATER

Drug Facts

ACTIVE INGREDIENT

Sodium Monofluorophosphate 0.74%

INACTIVE INGREDIENT

D-Sorbitol Solution, Concentrated Glycerin, Water, Silicon Dioxide, Sodium Lauryl Sulfate, Jasmine Flavor, Xylitol, Sodium Carboxymethylcellulose, Enzymatically Modified Stevia, Jasmine Mint Flavor, Titanium Oxide, Spearmint Oil, Aluminium Chlorohydroxy Allantoinate, Hydroxyapatite, L-Menthol, Propolis Extract10, Matricaria Extract, Green Tea Extract, Aloe Extract, Rosemary Extract, Grapefruit Extract, Taraxacum, officinale Extract, Clove extract, Moutan Root Extract

PURPOSE

Caries prevention

WARNINGS

■ Contains 977ppm of fluoride.
■ Do not swallow and rinse mouth thoroughly after use
■ If you experience any problems with your gums or mouth during use, discontinue use and consult your doctor.
■ For children under 6 years of age, use small amounts of toothpaste. And use it under the supervision of a guardian to avoid sucking or swallowing.
■ Consult a physician or dentist immediately if a child under 6 years old has swallowed large quantities.
■ Keep out of the reach of children under 6 years of age.

KEEP OUT OF REACH OF CHILDREN

■ Keep out of the reach of children under 6 years of age.

Uses

■ Keep your mouth clean.
■ Prevents tooth decay caused by fluoride and removes bad breath.
■ Increases aesthetic effect.
■ Prevention of plaque deposition, removal of plaque (anti-prag)

Directions

■ Brushing the teeth with a suitable amount

Other information

■ Airtight container, Store in normal temperature (1~30℃)